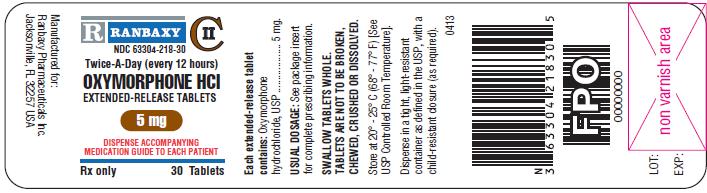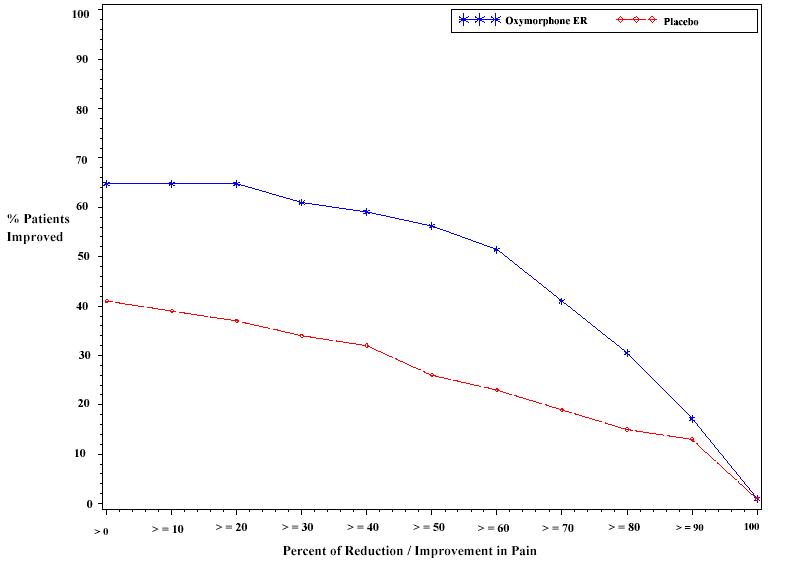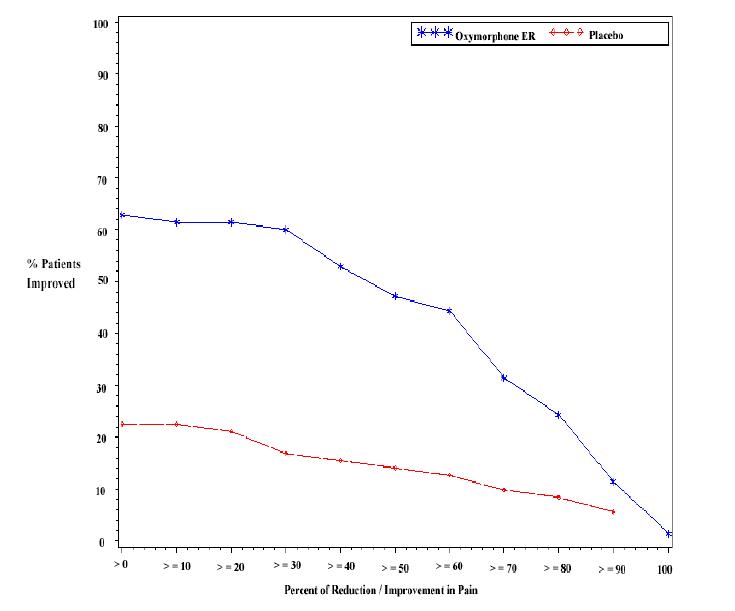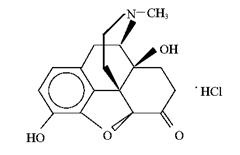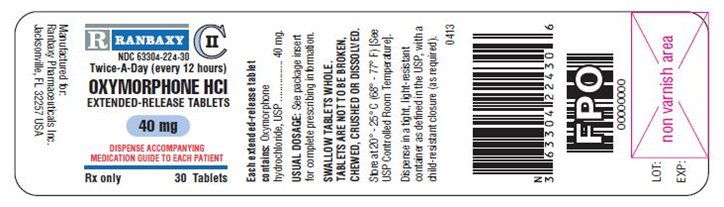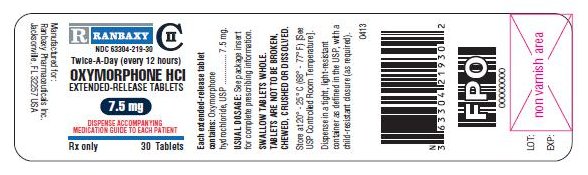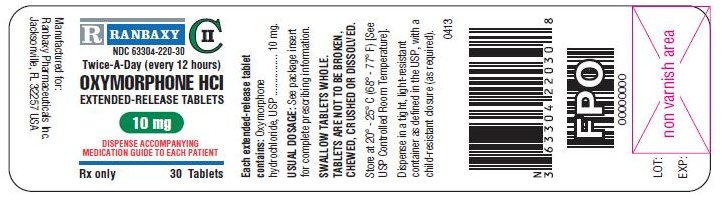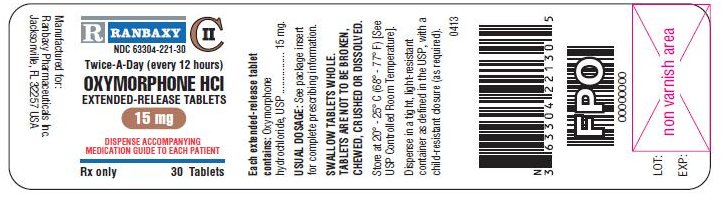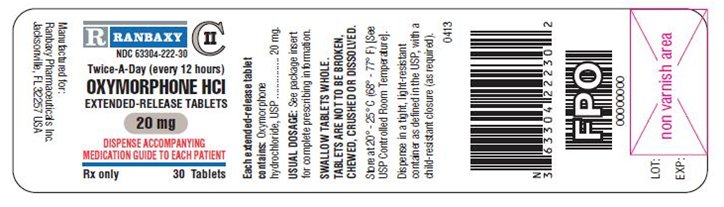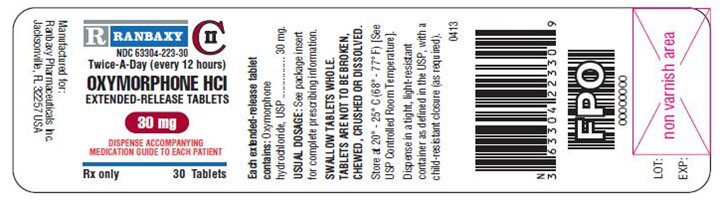 DRUG LABEL: Oxymorphone hydrochloride
NDC: 63304-218 | Form: TABLET, FILM COATED, EXTENDED RELEASE
Manufacturer: Ranbaxy Pharmaceuticals Inc.
Category: prescription | Type: HUMAN PRESCRIPTION DRUG LABEL
Date: 20160913
DEA Schedule: CII

ACTIVE INGREDIENTS: OXYMORPHONE HYDROCHLORIDE 5 mg/1 1
INACTIVE INGREDIENTS: HYPROMELLOSES; POLYETHYLENE GLYCOLS; CELLULOSE, MICROCRYSTALLINE; SODIUM STEARYL FUMARATE; TALC; TITANIUM DIOXIDE; FD&C RED NO. 40; SILICON DIOXIDE; POLYVINYL ALCOHOL

HIGHLIGHTS OF PRESCRIBING INFORMATION

These highlights do not include all the information needed to use OXYMORPHONE hydrochloride Extended-Release Tablets safely and effectively. See full prescribing information for OXYMORPHONE hydrochloride Extended-Release Tablets.
OXYMORPHONE hydrochloride Extended-Release Tablets, for oral use, CII
Initial U.S. Approval: 1959

WARNING: ADDICTION, ABUSE, AND MISUSE; LIFE-THREATENING RESPIRATORY DEPRESSION; ACCIDENTAL INGESTION; NEONATAL OPIOID WITHDRAWAL SYNDROME; and INTERACTION WITH ALCOHOL

See full prescribing information for complete boxed warning.

- Oxymorphone hydrochloride extended-release tablets expose users to risks of addiction, abuse, and misuse, which can lead to overdose and death. Assess each patient’s risk before prescribing, and monitor regularly for development of these behaviors or conditions. (5.1)
- Serious life-threatening or fatal respiratory depression may occur. Monitor closely, especially upon initiation or following a dose increase. Instruct patients to swallow oxymorphone hydrochloride extended-release tablets whole to avoid exposure to a potentially fatal dose of oxymorphone. (5.2)
- Accidental ingestion of oxymorphone hydrochloride extended-release tablets, especially in children, can result in fatal overdose of oxymorphone. (5.2)
- Prolonged use of oxymorphone hydrochloride extended-release tablets during pregnancy can result in neonatal opioid withdrawal syndrome, which may be life-threatening if not recognized and treated. If opioid use is required for a prolonged period in a pregnant woman, advise the patient of the risk of neonatal opioid withdrawal syndrome and ensure that appropriate treatment will be available (5.3).
- Instruct patients not to consume alcohol or any product containing alcohol while taking oxymorphone hydrochloride extended-release tablets because co-ingestion can result in fatal plasma oxymorphone levels. (5.4)

RECENT MAJOR CHANGES

Boxed Warning 4/2014

Indications and Usage (1) 4/2014

Dosage and Administration (2) 4/2014

Warnings and Precautions (5) 4/2014

1 INDICATIONS AND USAGE

Oxymorphone hydrochloride extended-release tablets are an opioid agonist indicated for the management of pain severe enough to require daily, around-the-clock, long-term opioid treatment and for which alternative treatment options are inadequate. (1)

Limitations of Use

- Because of the risks of addiction, abuse, and misuse with opioids, even at recommended doses, and because of the greater risks of overdose and death with extended-release opioid formulations, reserve oxymorphone hydrochloride extended-release tablets for use in patients for whom alternative treatment options (e.g., non-opioid analgesics or immediate-release opioids) are ineffective, not tolerated, or would be otherwise inadequate to provide sufficient management of pain. (1)
- Oxymorphone hydrochloride extended-release tablets are not indicated as an as-needed (prn) analgesic. (1)

2 DOSAGE AND ADMINISTRATION

- For opioid-naïve and opioid non-tolerant patients, initiate with 5 mg tablets orally every 12 hours. (2.1)
- To convert to oxymorphone hydrochloride extended-release tablets from another opioid, use available conversion factors to obtain estimated dose. (2.1)
- Dose can be increased every 3 to 7 days, using increments of 5 to 10 mg every 12 hours (i.e., 10 to 20 mg per day). (2.2)
- Administer on an empty stomach, at least 1 hour prior to or 2 hours after eating. (2.1)
- Do not abruptly discontinue oxymorphone hydrochloride extended-release tablets in a physically dependent patient. (2.3, 5.15)
- Instruct patients to swallow oxymorphone hydrochloride extended-release tablets intact. (2.4)
- Reduce the dose of oxymorphone hydrochloride extended-release tablets in patients with mild hepatic impairment and patients with renal impairment. (2.5, 2.6)

3 DOSAGE FORMS AND STRENGTHS

- Extended-release tablets: 5 mg, 7.5 mg, 10 mg, 15 mg, 20 mg, 30 mg, and 40 mg

4 CONTRAINDICATIONS

- Significant respiratory depression (4)
- Acute or severe bronchial asthma (4)
- Known or suspected paralytic ileus (4)
- Hypersensitivity to oxymorphone (4)
- Moderate or severe hepatic impairment (4)

5 WARNINGS AND PRECAUTIONS

See Boxed WARNINGS

- Interaction with CNS depressants: Concomitant use may cause profound sedation, respiratory depression, and death. If coadministration is required, consider dose reduction of one or both drugs because of additive pharmacological effects. (5.4, 7.2)
- Elderly, cachectic, and debilitated patients and those with chronic pulmonary disease: Monitor closely because of increased risk for life-threatening respiratory depression. (5.5, 5.6)
- Anaphylaxis, Angioedema, and Other Hypersensitivity Reactions: If symptoms occur, stop administration immediately, discontinue permanently, and do not rechallenge with any other oxymorphone formulation. (5.7)
- Adrenal Insufficiency: If diagnosed, treat with physiologic replacement of corticosteroids, and wean patient off of the opioid. (5.8)
- Hypotensive effect: Monitor during dose initiation and titration. (5.10)
- Patients with head injury or increased intracranial pressure: Monitor for sedation and respiratory depression. Avoid use of oxymorphone hydrochloride extended-release tablets in patients with impaired consciousness or coma susceptible to intracranial effects of CO2 retention. (5.11)

6 ADVERSE REACTIONS

Adverse reactions in ≥ 2% of patients in placebo-controlled trials: nausea, constipation, dizziness, somnolence, vomiting, pruritus, headache, sweating increased, dry mouth, sedation, diarrhea, insomnia, fatigue, appetite decreased, and abdominal pain. (6.1)

To report SUSPECTED ADVERSE REACTIONS, contact Ranbaxy Pharmaceuticals Inc. at 1-888-Ranbaxy (726-2299) or FDA at 1-800-FDA-1088 or www.fda.gov/medwatch.

7 DRUG INTERACTIONS

- Serotonergic Drugs: Concomitant use may result in serotonin syndrome. Discontinue oxymorphone hydrochloride extended-release tablets if serotonin syndrome is suspected. (7.3)
- Mixed agonist/antagonist and partial agonist opioid analgesics: Avoid use with oxymorphone hydrochloride extended-release tablets because they may reduce analgesic effect of oxymorphone hydrochloride extended-release tablets or precipitate withdrawal symptoms. (7.4)

8 USE IN SPECIFIC POPULATIONS

- Pregnancy: Based on animal data, may cause fetal harm. (8.1)
- Nursing mothers: Closely monitor infants of nursing women receiving oxymorphone hydrochloride extended-release tablets. (8.3)

FULL PRESCRIBING INFORMATION

WARNING: ADDICTION, ABUSE, AND MISUSE; LIFE-THREATENING RESPIRATORY DEPRESSION; ACCIDENTAL INGESTION; NEONATAL OPIOID WITHDRAWAL SYNDROME; and INTERACTION WITH ALCOHOL

Addiction, Abuse, and Misuse
Oxymorphone hydrochloride extended-release tablets expose patients and other users to the risks of opioid addiction, abuse, and misuse, which can lead to overdose and death. Assess each patient’s risk prior to prescribing oxymorphone hydrochloride extended-release tablets and monitor all patients regularly for the development of these behaviors or conditions [see Warnings and Precautions (5.1)].
Life-threatening Respiratory Depression
Serious, life-threatening, or fatal respiratory depression may occur with use of oxymorphone hydrochloride extended-release tablets. Monitor for respiratory depression, especially during initiation of oxymorphone hydrochloride extended-release tablets or following a dose increase. Instruct patients to swallow oxymorphone hydrochloride extended-release tablets whole; crushing, chewing, or dissolving oxymorphone hydrochloride extended-release tablets can cause rapid release and absorption of a potentially fatal dose of oxymorphone [see Warnings and Precautions (5.2)].
Accidental Ingestion
Accidental ingestion of even one dose of oxymorphone hydrochloride extended-release tablets, especially by children, can result in a fatal overdose of oxymorphone [see Warnings and Precautions (5.2)].
Neonatal Opioid Withdrawal Syndrome
Prolonged use of oxymorphone hydrochloride extended-release tablets during pregnancy can result in neonatal opioid withdrawal syndrome, which may be life-threatening if not recognized and treated, and requires management according to protocols developed by neonatology experts. If opioid use is required for a prolonged period in a pregnant woman, advise the patient of the risk of neonatal opioid withdrawal syndrome and ensure that appropriate treatment will be available [see Warnings and Precautions (5.3)].
Interaction with Alcohol
Instruct patients not to consume alcoholic beverages or use prescription or non-prescription products that contain alcohol while taking oxymorphone hydrochloride extended-release tablets. The co-ingestion of alcohol with oxymorphone hydrochloride extended-release tablets may result in increased plasma levels and a potentially fatal overdose of oxymorphone [see Warnings and Precautions (5.4)].

WARNING: RISKS FROM CONCOMITANT USE WITH BENZODIAZEPINES OR OTHER CNS DEPRESSANTS

Risks From Concomitant Use With Benzodiazepines Or Other CNS Depressants

Concomitant use of opioids with benzodiazepines or other central nervous system (CNS) depressants, including alcohol, may result in profound sedation, respiratory depression, coma, and death [see Warnings and Precautions (5.4), Drug Interactions (7.2)].

• Reserve concomitant prescribing of oxymorphone hydrochloride extended-release tablets and benzodiazepines or other CNS depressants for use in patients for whom alternative treatment options are inadequate.

• Limit dosages and durations to the minimum required.

• Follow patients for signs and symptoms of respiratory depression and sedation.

1 INDICATIONS AND USAGE

Oxymorphone hydrochloride extended-release tablets are indicated for the management of pain severe enough to require daily, around-the-clock, long-term opioid treatment and for which alternative treatment options are inadequate.

Limitations of Usage

Because of the risks of addiction, abuse, and misuse with opioids, even at recommended doses, and because of the greater risks of overdose and death with extended-release opioid formulations, reserve oxymorphone hydrochloride extended-release tablets for use in patients for whom alternative treatment options (e.g., non-opioid analgesics or immediate-release opioids) are ineffective, not tolerated, or would be otherwise inadequate to provide sufficient management of pain.

Oxymorphone hydrochloride extended-release tablets are not indicated as an as-needed (prn) analgesic.

2 DOSAGE AND ADMINISTRATION

2.1 Initial Dosing

To avoid medication errors, prescribers and pharmacists must be aware that oxymorphone is available as both immediate-release 5 mg and 10 mg tablets and extended-release 5 mg and 10 mg tablets [see Dosage Forms and Strengths].

Oxymorphone hydrochloride extended-release tablets should be prescribed only by healthcare professionals who are knowledgeable in the use of potent opioids for the management of chronic pain.

Initiate the dosing regimen for each patient individually, taking into account the patient’s prior analgesic treatment experience and risk factors for addiction, abuse, and misuse [see Warnings and Precautions (5.1)]. Monitor patients closely for respiratory depression, especially within the first 24 to 72 hours of initiating therapy with oxymorphone hydrochloride extended-release tablets [see Warnings and Precautions (5.2)].

Oxymorphone hydrochloride extended-release tablets must be taken whole, one tablet at a time, with enough water to ensure complete swallowing immediately after placing in the mouth [see Patient Counseling Information (17)]. Crushing, chewing, or dissolving oxymorphone hydrochloride extended-release tablets will result in uncontrolled delivery of oxymorphone and can lead to overdose or death [see Warnings and Precautions (5.2)].

Oxymorphone hydrochloride extended-release tablets are administered at a frequency of twice daily (every 12 hours). Administer on an empty stomach, at least 1 hour prior to or 2 hours after eating.

Use of Oxymorphone Hydrochloride Extended-Release Tablets as the First Opioid Analgesic

Initiate treatment with oxymorphone hydrochloride extended-release tablets with the 5 mg tablet orally every 12-hours.

Use of Oxymorphone Hydrochloride Extended-Release Tablets in Patients who are not Opioid Tolerant

The starting dose for patients who are not opioid tolerant is oxymorphone hydrochloride extended-release tablets 5 mg orally every 12 hours. Patients who are opioid tolerant are those receiving, for one week or longer, at least 60 mg oral morphine per day, 25 mcg transdermal fentanyl per hour, 30 mg oral oxycodone per day, 8 mg oral hydromorphone per day, 25 mg oral oxymorphone per day, or an equianalgesic dose of another opioid.

Use of higher starting doses in patients who are not opioid tolerant may cause fatal respiratory depression.

Conversion from Oxymorphone Hydrochloride Tablets to Oxymorphone Hydrochloride Extended-Release Tablets

Patients receiving oxymorphone hydrochloride tablets may be converted to oxymorphone hydrochloride extended-release tablets by administering half the patient's total daily oral oxymorphone hydrochloride dose as oxymorphone hydrochloride extended-release tablets, every 12 hours.

Conversion from Parenteral Oxymorphone to Oxymorphone Hydrochloride Extended-Release Tablets

The absolute oral bioavailability of oxymorphone hydrochloride extended-release tablets is approximately 10%. Convert patients receiving parenteral oxymorphone to oxymorphone hydrochloride extended-release tablets by administering 10 times the patient's total daily parenteral oxymorphone dose as oxymorphone hydrochloride extended-release tablets in two equally divided doses (e.g., [IV dose x 10] divided by 2). Due to patient variability with regards to opioid analgesic response, upon conversion monitor patients closely to evaluate for adequate analgesia and side effects.

Conversion from Other Oral Opioids to Oxymorphone Hydrochloride Extended-Release Tablets

Discontinue all other around-the-clock opioid drugs when oxymorphone hydrochloride extended-release tablets therapy is initiated.

While there are useful tables of opioid equivalents readily available, there is substantial inter-patient variability in the relative potency of different opioid drugs and products. As such, it is preferable to underestimate a patient’s 24-hour oral oxymorphone hydrochloride extended-release tablets requirements and provide rescue medication (e.g., immediate-release opioid) than to overestimate the 24-hour oral oxymorphone hydrochloride extended-release tablets requirements which could result in adverse reactions. In an oxymorphone clinical trial with an open-label titration period, patients were converted from their prior opioid to oxymorphone hydrochloride extended-release tablets using Table 1 as a guide for the initial oxymorphone hydrochloride extended-release tablets dose.

Consider the following when using the information in Table 1:

- This is not a table of equianalgesic doses.
- The conversion factors in this table are only for the conversion from one of the listed oral opioid analgesics to oxymorphone hydrochloride extended-release tablets.
- This table cannot be used to convert from oxymorphone hydrochloride extended-release tablets to another opioid. Doing so will result in an over-estimation of the dose of the new opioid and may result in fatal overdose.

CONVERSION FACTORS TO OXYMORPHONE HYDROCHLORIDE EXTENDED-RELEASE TABLETS
Prior Oral Opioid | Approximate Oral Conversion Factor
Oxymorphone | 1
Hydrocodone | 0.5
Oxycodone | 0.5
Methadone | 0.5
Morphine | 0.333

To calculate the estimated oxymorphone hydrochloride extended-release tablets dose using Table 1:

- For patients on a single opioid, sum the current total daily dose of the opioid and then multiply the total daily dose by the conversion factor to calculate the approximate oral (active opioid) daily dose.
- For patients on a regimen of more than one opioid, calculate the approximate oral (active opioid) dose for each opioid and sum the totals to obtain the approximate total (active opioid) daily dose.
- For patients on a regimen of fixed-ratio opioid/non-opioid analgesic products, use only the opioid component of these products in the conversion

Always round the dose down, if necessary, to the appropriate oxymorphone hydrochloride extended-release tablets strength(s) available.

Example conversion from a single opioid to oxymorphone hydrochloride extended-release tablets:

Step 1: Sum the total daily dose of the opioid oxycodone 20 mg BID 20 mg former opioid 2 times daily = 40 mg total daily dose of former opioid
Step 2: Calculate the approximate equivalent dose of oral (active opioid) based on the total daily dose of the current opioid using Table 1 40 mg total daily dose of former opioid x 0.5 mg Conversion Factor = 20 mg of oral (active opioid) daily
Step 3: Calculate the approximate starting dose of oxymorphone hydrochloride extended-release tablets to be given every 12 hours. Round down, if necessary, to the appropriate oxymorphone hydrochloride extended-release tablets strengths available. 10 mg oxymorphone hydrochloride extended-release tablets every 12 hours

Conversion from Methadone to Oxymorphone Hydrochloride Extended-Release Tablets

Close monitoring is of particular importance when converting from methadone to other opioid agonists. The ratio between methadone and other opioid agonists may vary widely as a function of previous dose exposure. Methadone has a long half-life and can accumulate in the plasma.

2.2 Titration and Maintenance of Therapy

Individually titrate oxymorphone hydrochloride extended-release tablets to a dose that provides adequate analgesia and minimizes adverse reactions. Continually reevaluate patients receiving oxymorphone hydrochloride extended-release tablets to assess the maintenance of pain control and the relative incidence of adverse reactions, as well as monitoring for the development of addiction, abuse, and misuse. Frequent communication is important among the prescriber, other members of the healthcare team, the patient, and the caregiver/family during periods of changing analgesic requirements, including initial titration. During chronic therapy, periodically reassess the continued need for the use of opioid analgesics.

If the level of pain increases, attempt to identify the source of increased pain, while adjusting the oxymorphone hydrochloride extended-release tablets dose to decrease the level of pain. Because steady-state plasma concentrations are approximated within 3 days, oxymorphone hydrochloride extended-release tablets dosage adjustments, preferably at increments of 5 to 10 mg every 12 hours, may be done every 3 to 7 days.

Patients who experience breakthrough pain may require a dose increase of oxymorphone hydrochloride extended-release tablets, or may need rescue medication with an appropriate dose of an immediate-release analgesic. If the level of pain increases after dose stabilization, attempt to identify the source of increased pain before increasing oxymorphone hydrochloride extended-release tablets dose.

If unacceptable opioid-related adverse reactions are observed, the subsequent dose may be reduced. Adjust the dose to obtain an appropriate balance between management of pain and opioid-related adverse reactions.

2.3 Discontinuation of Oxymorphone Hydrochloride Extended-Release Tablets

When a patient no longer requires therapy with oxymorphone hydrochloride extended-release tablets, use a gradual downward titration of the dose every two to four days, to prevent signs and symptoms of withdrawal in the physically-dependent patient. Do not abruptly discontinue oxymorphone hydrochloride extended-release tablets.

2.4 Administration of Oxymorphone Hydrochloride Extended-Release Tablets

Instruct patients to swallow oxymorphone hydrochloride extended-release tablets intact. The tablets are not to be crushed, dissolved, or chewed due to the risk of rapid release and absorption of a potentially fatal dose of oxymorphone [see Warnings and Precautions (5.2)]. Administer on an empty stomach, at least 1 hour prior to or 2 hours after eating.

2.5 Patients with Hepatic Impairment

Oxymorphone hydrochloride extended-release tablets are contraindicated in patients with moderate or severe hepatic impairment.

In opioid-naïve patients with mild hepatic impairment, initiate treatment with the 5 mg dose. For patients on prior opioid therapy, start oxymorphone hydrochloride extended-release tablets at 50% lower than the starting dose for a patient with normal hepatic function on prior opioids and titrate slowly. Monitor patients closely for signs of respiratory or central nervous system depression [see Warnings and Precautions (5.2), Use in Specific Populations (8.6) and Clinical Pharmacology (12.3)].

2.6 Patients with Renal Impairment

In patients with creatinine clearance rates less than 50 mL/min, start oxymorphone hydrochloride extended-release tablets in the opioid-naïve patient with the 5 mg dose. For patients on prior opioid therapy, start oxymorphone hydrochloride extended-release tablets at 50% lower than the starting dose for a patient with normal renal function on prior opioids and titrate slowly. Monitor patients closely for signs of respiratory or central nervous system depression [see Warnings and Precautions (5.2), Use in Specific Populations (8.7) and Clinical Pharmacology (12.3)].

2.7 Geriatric Patients

The steady-state plasma concentrations of oxymorphone are approximately 40% higher in elderly subjects than in young subjects. Initiate dosing with oxymorphone hydrochloride extended-release tablets in patients 65 years of age and over using the 5 mg dose and monitor closely for signs of respiratory and central nervous system depression when initiating and titrating oxymorphone hydrochloride extended-release tablets to adequate analgesia [see Warnings and Precautions (5.2), Use in Specific Populations (8.5) and Clinical Pharmacology (12.3)]. For patients on prior opioid therapy, start oxymorphone hydrochloride extended-release tablets at 50% lower than the starting dose for a younger patient on prior opioids and titrate slowly.

3 DOSAGE FORMS AND STRENGTHS

The 5 mg dosage form is pink to light pink, round, biconvex film-coated tablet, debossed with ‘RH 29’ on one side and plain on the other side.

The 7.5 mg dosage form is gray to light gray, round, biconvex film-coated tablet, debossed with ‘RI 36’ on one side and plain on the other side.

The 10 mg dosage form is orange to light orange, round, biconvex film-coated tablet, debossed with ‘RH 30’ on one side and plain on the other side.

The 15 mg dosage form is white to off-white, round, biconvex film-coated tablet, debossed with ‘RI 37’ on one side and plain on the other side.

The 20 mg dosage form is green to light green, round, biconvex film-coated tablet, debossed with ‘RH 31’ on one side and plain on the other side.

The 30 mg dosage form is reddish brown, round, biconvex film-coated tablet, debossed with ‘RI 38’ on one side and plain on the other side.

The 40 mg dosage form is yellow to light yellow, round, biconvex film-coated tablet, debossed with ‘RH 32’ on one side and plain on the other side.

4 CONTRAINDICATIONS

Oxymorphone hydrochloride extended-release tablets are contraindicated in patients with:

- Significant respiratory depression
- Acute or severe bronchial asthma or hypercarbia
- Known or suspected paralytic ileus
- Moderate and severe hepatic impairment [see Clinical Pharmacology (12.3), Warnings and Precautions (5.9)].
- Hypersensitivity (e.g. anaphylaxis) to oxymorphone, any other ingredients in oxymorphone hydrochloride extended-release tablets, or to morphine analogs such as codeine [see Adverse Reactions (6.1)].

5 WARNINGS AND PRECAUTIONS

5.1 Addiction, Abuse, and Misuse

Oxymorphone hydrochloride extended-release tablets contain oxymorphone, a Schedule II controlled substance. As an opioid, oxymorphone hydrochloride extended-release tablets expose users to the risks of addiction, abuse, and misuse [see Drug Abuse and Dependence (9)]. As modified-release products such as oxymorphone hydrochloride extended-release tablets deliver the opioid over an extended period of time, there is a greater risk for overdose and death due to the larger amount of oxymorphone present.

Although the risk of addiction in any individual is unknown, it can occur in patients appropriately prescribed oxymorphone hydrochloride extended-release tablets and in those who obtain the drug illicitly. Addiction can occur at recommended doses and if the drug is misused or abused.

Assess each patient’s risk for opioid abuse or addiction, abuse, or misuse prior to prescribing oxymorphone hydrochloride extended-release tablets and monitor all patients receiving oxymorphone hydrochloride extended-release tablets for the development of these behaviors or conditions. Risks are increased in patients with a personal or family history of substance abuse (including drug or alcohol addiction or abuse) or mental illness (e.g., major depression). The potential for these risks should not, however, prevent the prescribing of oxymorphone hydrochloride extended-release tablets for the proper management of pain in any given patient. Patients at increased risk may be prescribed modified-release opioid formulations such as oxymorphone hydrochloride extended-release tablets, but use in such patients necessitates intensive counseling about the risks and proper use of oxymorphone hydrochloride extended-release tablets along with intensive monitoring for signs of addiction, abuse, and misuse.

Abuse, or misuse of oxymorphone hydrochloride extended-release tablets by crushing, chewing, snorting, or injecting the dissolved product will result in the uncontrolled delivery of the oxymorphone and can result in overdose and death [see Overdosage (10)].

Opioid agonists such as oxymorphone hydrochloride extended-release tablets are sought by drug abusers and people with addiction disorders and are subject to criminal diversion. Consider these risks when prescribing or dispensing oxymorphone hydrochloride extended-release tablets. Strategies to reduce these risks include prescribing the drug in the smallest appropriate quantity and advising the patient on the proper disposal of unused drug [see Patient Counseling Information (17)]. Contact local state professional licensing board or state controlled substances authority for information on how to prevent and detect abuse or diversion of this product.

5.2 Life Threatening Respiratory Depression

Serious, life-threatening, or fatal respiratory depression has been reported with the use of modified-release opioids, even when used as recommended. Respiratory depression from opioid use, if not immediately recognized and treated, may lead to respiratory arrest and death. Management of respiratory depression may include close observation, supportive measures, and use of opioid antagonists, depending on the patient’s clinical status [see Overdosage (10)]. Carbon dioxide (CO2) retention from opioid-induced respiratory depression can exacerbate the sedating effects of opioids.

While serious, life-threatening, or fatal respiratory depression can occur at any time during the use of oxymorphone hydrochloride extended-release tablets, the risk is greatest during the initiation of therapy or following a dose increase. Closely monitor patients for respiratory depression when initiating therapy with oxymorphone hydrochloride extended-release tablets and following dose increases.

To reduce the risk of respiratory depression, proper dosing and titration of oxymorphone hydrochloride extended-release tablets are essential [see Dosage and Administration (2.1, 2.2)]. Overestimating the oxymorphone hydrochloride extended-release tablets dose when converting patients from another opioid product can result in fatal overdose with the first dose.

Accidental ingestion of even one dose of oxymorphone hydrochloride extended-release tablets dose, especially by children, can result in respiratory depression and death due to an overdose of oxymorphone.

5.3 Neonatal Opioid Withdrawal Syndrome

Prolonged use of oxymorphone hydrochloride extended-release tablets during pregnancy can result in withdrawal signs in the neonate. Neonatal opioid withdrawal syndrome, unlike opioid withdrawal syndrome in adults, may be life-threatening if not recognized and treated, and requires management according to protocols developed by neonatology experts. If opioid use is required for a prolonged period in a pregnant woman, advise the patient of the risk of neonatal opioid withdrawal syndrome and ensure that appropriate treatment will be available.

Neonatal opioid withdrawal syndrome presents as irritability, hyperactivity and abnormal sleep pattern, high pitched cry, tremor, vomiting, diarrhea and failure to gain weight. The onset, duration, and severity of neonatal opioid withdrawal syndrome vary based on the specific opioid used, duration of use, timing and amount of last maternal use, and rate of elimination of the drug by the newborn.

5.4 Risks from Concomitant Use with Benzodiazepines or Other CNS Depressants

Profound sedation, respiratory depression, coma, and death may result from the concomitant use of oxymorphone hydrochloride with benzodiazepines or other CNS depressants (e.g., non-benzodiazepine sedatives/hypnotics, anxiolytics, tranquilizers, muscle relaxants, general anesthetics, antipsychotics, other opioids, alcohol). Because of these risks, reserve concomitant prescribing of these drugs for use in patients for whom alternative treatment options are inadequate.

Observational studies have demonstrated that concomitant use of opioid analgesics and benzodiazepines increases the risk of drug-related mortality compared to use of opioid analgesics alone. Because of similar pharmacological properties, it is reasonable to expect similar risk with the concomitant use of other CNS depressant drugs with opioid analgesics [see Drug Interactions (7)].

If the decision is made to prescribe a benzodiazepine or other CNS depressant concomitantly with an opioid analgesic, prescribe the lowest effective dosages and minimum durations of concomitant use. In patients already receiving an opioid analgesic, prescribe a lower initial dose of the benzodiazepine or other CNS depressant than indicated in the absence of an opioid, and titrate based on clinical response. If an opioid analgesic is initiated in a patient already taking a benzodiazepine or other CNS depressant, prescribe a lower initial dose of the opioid analgesic, and titrate based on clinical response. Follow patients closely for signs and symptoms of respiratory depression and sedation.

Advise both patients and caregivers about the risks of respiratory depression and sedation when oxymorphone hydrochloride is used with benzodiazepines or other CNS depressants (including alcohol and illicit drugs). Advise patients not to drive or operate heavy machinery until the effects of concomitant use of the benzodiazepine or other CNS depressant have been determined. Screen patients for risk of substance use disorders, including opioid abuse and misuse, and warn them of the risk for overdose and death associated with the use of additional CNS depressants including alcohol and illicit drugs [see Drug Interactions (7) and Patient Counseling Information (17)].

5.5 Use in Elderly, Cachectic, and Debilitated Patients

Life-threatening respiratory depression is more likely to occur in elderly, cachectic, or debilitated patients as they may have altered pharmacokinetics or altered clearance compared to younger, healthier patients. Monitor such patients closely, particularly when initiating and titrating oxymorphone hydrochloride extended-release tablets and when oxymorphone hydrochloride extended-release tablets are given concomitantly with other drugs that depress respiration [see Warnings and Precautions (5.2)].

5.6 Use in Patients with Chronic Pulmonary Disease

Monitor patients with significant chronic obstructive pulmonary disease or cor pulmonale, and patients having a substantially decreased respiratory reserve, hypoxia, hypercapnia, or pre-existing respiratory depression for respiratory depression, particularly when initiating therapy and titrating with oxymorphone hydrochloride extended-release tablets, as in these patients, even usual therapeutic doses of oxymorphone hydrochloride extended-release tablets may decrease respiratory drive to the point of apnea [see Warnings and Precautions (5.2)]. Consider the use of alternative non-opioid analgesics in these patients if possible.

5.7 Anaphylaxis, Angioedema, and Other Hypersensitivity Reactions

Potentially life-threatening hypersensitivity reactions, including anaphylaxis and angioedema, have occurred in patients treated with oxymorphone hydrochloride extended-release tablets in the postmarket setting. The most commonly described clinical features in these reports were swelling of the face, eyes, mouth, lips, tongue, hands, and/or throat; dyspnea; hives, pruritus, and/or rash; and nausea/vomiting. If anaphylaxis or other hypersensitivity occurs, stop administration of oxymorphone hydrochloride extended-release tablets immediately, discontinue oxymorphone hydrochloride extended-release tablets permanently, and do not rechallenge with any formulation of oxymorphone. Advise patients to seek immediate medical attention if they experience any symptoms of a hypersensitivity reaction [see Patient Counseling Information (17)].

5.8 Adrenal Insufficiency

Cases of adrenal insufficiency have been reported with opioid use, more often following greater than one 1 month of use. Presentation of adrenal insufficiency may include non-specific symptoms and signs including nausea, vomiting, anorexia, fatigue, weakness, dizziness, and low blood pressure. If adrenal insufficiency is suspected, confirm the diagnosis with diagnostic testing as soon as possible. If adrenal insufficiency is diagnosed, treat with physiologic replacement doses of corticosteroids. Wean the patient off of the opioid to allow adrenal function to recover and continue corticosteroid treatment until adrenal function recovers. Other opioids may be tried as some cases reported use of a different opioid without recurrence of adrenal insufficiency. The information available does not identify any particular opioids as being more likely to be associated with adrenal insufficiency.

5.9 Use in Patients with Hepatic Impairment

A study of oxymorphone hydrochloride extended-release tablets in patients with hepatic disease indicated greater plasma concentrations than those with normal hepatic function [see Clinical Pharmacology (12.3)]. Oxymorphone hydrochloride extended-release tablets are contraindicated in patients with moderate or severe hepatic impairment. In patients with mild hepatic impairment reduce the starting dose to the lowest dose and monitor for signs of respiratory and central nervous system depression [see Dosage and Administration (2.5)].

5.10 Hypotensive Effect

Oxymorphone hydrochloride extended-release tablets may cause severe hypotension including orthostatic hypotension and syncope in ambulatory patients. There is an increased risk in patients whose ability to maintain blood pressure has already been compromised by a reduced blood volume or concurrent administration of certain CNS depressant drugs (e.g. phenothiazines or general anesthetics) [see Drug Interactions (7.2)]. Monitor these patients for signs of hypotension after initiating or titrating the dose of oxymorphone hydrochloride extended-release tablets. In patients with circulatory shock, oxymorphone hydrochloride extended-release tablets may cause vasodilation that can further reduce cardiac output and blood pressure. Avoid the use of oxymorphone hydrochloride extended-release tablets in patients with circulatory shock.

5.11 Use in Patients with Head Injury or Increased Intracranial Pressure

Monitor patients taking oxymorphone hydrochloride extended-release tablets who may be susceptible to the intracranial effects of CO2 retention (e.g., those with evidence of increased intracranial pressure or brain tumors) for signs of sedation and respiratory depression, particularly when initiating therapy with oxymorphone hydrochloride extended-release tablets. Oxymorphone hydrochloride extended-release tablets may reduce respiratory drive, and the resultant CO2 retention can further increase intracranial pressure. Opioids may also obscure the clinical course in a patient with a head injury. Avoid the use of oxymorphone hydrochloride extended-release tablets in patients with impaired consciousness or coma.

5.12 Use in Patients with Gastrointestinal Conditions

Oxymorphone hydrochloride extended-release tablets are contraindicated in patients with paralytic ileus. Avoid the use of oxymorphone hydrochloride extended-release tablets in patients with other GI obstruction.

The oxymorphone in oxymorphone hydrochloride extended-release tablets may cause spasm of the sphincter of Oddi. Monitor patients with biliary tract disease, including acute pancreatitis, for worsening symptoms. Opioids may cause increases in the serum amylase.

5.13 Use in Patients with Convulsive or Seizure Disorders

The oxymorphone in oxymorphone hydrochloride extended-release tablets may aggravate convulsions in patients with convulsive disorders, and may induce or aggravate seizures in some clinical settings. Monitor patients with a history of seizure disorders for worsened seizure control during oxymorphone hydrochloride extended-release tablets therapy.

5.14 Avoidance of Withdrawal

Avoid the use of mixed agonist/antagonist (i.e., pentazocine, nalbuphine, and butorphanol) and partial agonist (buprenorphine) analgesics in patients who have received or are receiving a course of therapy with an opioid agonist analgesic, including oxymorphone hydrochloride extended-release tablets. In these patients, mixed agonists/antagonist and partial agonist analgesics may reduce the analgesic effect and/or may precipitate withdrawal symptoms.

When discontinuing oxymorphone hydrochloride extended-release tablets, gradually taper the dose [see Dosage and Administration (2.3)]. Do not abruptly discontinue oxymorphone hydrochloride extended-release tablets.

5.15 Driving and Operating Machinery

Oxymorphone hydrochloride extended-release tablets may impair the mental or physical abilities needed to perform potentially hazardous activities such as driving a car or operating machinery. Warn patients not to drive or operate dangerous machinery unless they are tolerant to the effects of oxymorphone hydrochloride extended-release tablets and know how they will react to the medication.

6 ADVERSE REACTIONS

The following serious adverse reactions are discussed elsewhere in the labeling:

- Addicition, Abuse, and Misuse [see Warnings and Precautions (5.1)]
- Life Threatening Respiratory Depression [see Warnings and Precautions (5.2)]
- Neonatal Opioid Withdrawal Syndrome [see Warnings and Precautions (5.3)]
- Interactions with Other CNS Depressants [see Warnings and Precautions (5.4)]
- Anaphylaxis, Angioedema, and Other Hypersensitivity Reactions [see Warnings and Precautions (5.7)]
- Adrenal Insufficiency [see Warnings and Precautions (5.8)]
- Hypotensive Effect [see Warnings and Precautions (5.10)]
- Gastrointestinal Effects [see Warnings and Precautions (5.12)]
- Seizures [see Warnings and Precautions (5.13)]

6.1 Clinical Trial Experience

Because clinical trials are conducted under widely varying conditions, adverse reaction rates observed in the clinical trials of a drug cannot be directly compared to rates in the clinical trials of another drug and may not reflect the rates observed in clinical practice.

The safety of oxymorphone hydrochloride extended-release tablets was evaluated in a total of 2011 patients in open-label and controlled clinical trials. The clinical trials enrolled of patients with moderate to severe chronic non-malignant pain, cancer pain, and post surgical pain. The most common serious adverse events reported with administration of oxymorphone hydrochloride extended-release tablets were chest pain, pneumonia and vomiting.

Tables 1 and 2 list the most frequently occurring adverse reactions (in at least 5% of patients) from the placebo-controlled trials in patients with low back pain.

Table 1: Treatment-Emergent Adverse Reactions Reported in ≥ 5% of Patients During the Open-Label Titration Period and Double-Blind Treatment Period by Preferred Term —Number (%) of Treated Patients (12-Week Study In Opioid-Naïve Patients with Low Back Pain)
 | Open-Label Titration Period | Double-Blind Treatment Period
 | Oxymorphone Hydrochloride Extended-Release Tablets | Oxymorphone Hydrochloride Extended-Release Tablets | Placebo
Preferred Term | (N = 325) | (N = 105) | (N = 100)
Constipation | 26% | 7% | 1%
Somnolence | 19% | 2% | 0%
Nausea | 18% | 11% | 9%
Dizziness | 11% | 5% | 3%
Headache | 11% | 4% | 2%
Pruritus | 7% | 3% | 1%

Table 2. Treatment-Emergent Adverse Reactions Reported in ≥ 5% of Patients During the Open-Label Titration Period and Double-Blind Treatment Period by Preferred Term —Number (%) of Treated Patients (12-Week Study In Opioid-Experienced Patients with Low Back Pain)
 | Open-Label Titration Period | Double-Blind Treatment Period
 | Oxymorphone Hydrochloride Extended-Release Tablets | Oxymorphone Hydrochloride Extended-Release Tablets | Placebo
Preferred Term | (N = 250) | (N = 70) | (N = 72)
Nausea | 20% | 3% | 1%
Constipation | 12% | 6% | 1%
Headache | 12% | 3% | 0%
Somnolence | 11% | 3% | 0%
Vomiting | 9% | 0% | 1%
Pruritus | 8% | 0% | 0%
Dizziness | 6% | 0% | 0%

The following table lists adverse reactions that were reported in at least 2% of patients in placebo-controlled trials (N = 5).

Table 3: Adverse Reactions Reported in Placebo-Controlled Clinical Trials with Incidence ≥ 2% in Patients Receiving Oxymorphone Hydrochloride Extended-Release Tablets.
MedDRA Preferred Term | Oxymorphone Hydrochloride Extended-Release Tablets (N = 1259) | Placebo (N = 461)
Nausea | 33% | 13%
Constipation | 28% | 13%
Dizziness (Excl Vertigo) | 18% | 8%
Somnolence | 17% | 2%
Vomiting | 16% | 4%
Pruritus | 15% | 8%
Headache | 12% | 6%
Sweating increased | 9% | 9%
Dry mouth | 6% | < 1%
Sedation | 6% | 8%
Diarrhea | 4% | 6%
Insomnia | 4% | 2%
Fatigue | 4% | 1%
Appetite decreased | 3% | < 1%
Abdominal pain | 3% | 2%

The common (≥ 1% to < 10%) adverse drug reactions reported at least once by patients treated with oxymorphone hydrochloride extended-release tablets in the clinical trials organized by MedDRA’s (Medical Dictionary for Regulatory Activities) System Organ Class and not represented in Table 1 were:

Eye disorders: vision blurred

Gastrointestinal disorders: diarrhea, abdominal pain, dyspepsia

General disorders and administration site conditions: dry mouth, appetite decreased, fatigue, lethargy, weakness, pyrexia, dehydration, weight decreased, edema

Nervous system disorders: insomnia

Psychiatric disorders: anxiety, confusion, disorientation, restlessness, nervousness, depression

Respiratory, thoracic and mediastinal disorders: dyspnea

Vascular disorders: flushing and hypertension

Other less common adverse reactions known with opioid treatment that were seen < 1% in the oxymorphone hydrochloride extended-release tablets trials include the following: Bradycardia, palpitation, syncope, tachycardia, postural hypotension, miosis, abdominal distention, ileus, hot flashes, allergic reactions, hypersensitivity, urticaria, oxygen saturation decreased, central nervous system depression, depressed level of consciousness, agitation, dysphoria, euphoric mood, hallucination, mental status changes, difficult micturition, urinary retention, hypoxia, respiratory depression, respiratory distress, clamminess, dermatitis, hypotension.

6.2 Post-marketing Experience

The following adverse reactions have been identified during post approval use of oxymorphone hydrochloride extended-release tablets. Because these reactions are reported voluntarily from a population of uncertain size, it is not always possible to reliably estimate their frequency or establish a causal relationship to drug exposure.

Nervous system disorder: amnesia, convulsion, memory impairment

Serotonin syndrome, adrenal insufficiency

Anaphylaxis, angioedema, and other hypersensitivity reactions

Androgen deficiency: Chronic use of opioids may influence the hypothalamic-pituitary-gonadal axis, leading to androgen deficiency that may manifest as low libido, impotence, erectile dysfunction, amenorrhea, or infertility. The causal role of opioids in the clinical syndrome of hypogonadism is unknown because the various medical, physical, lifestyle, and psychological stressors that may influence gonadal hormone levels have not been adequately controlled for in studies conducted to date. Patients presenting with symptoms of androgen deficiency should undergo laboratory evaluation.

7 DRUG INTERACTIONS

7.1 Alcohol

Concomitant use of alcohol with oxymorphone hydrochloride extended-release tablets can result in an increase of oxymorphone plasma levels and potentially fatal overdose of oxymorphone. Instruct patients not to consume alcoholic beverages or use prescription or non-prescription products containing alcohol while on oxymorphone hydrochloride extended-release tablets therapy [see Clinical Pharmacology (12.3)].

7.2 Benzodiazepines and other Central Nervous System (CNS) Depressants

Clinical Impact: | Due to additive pharmacologic effect, the concomitant use of benzodiazepines or other CNS depressants including alcohol, increases the risk of respiratory depression, profound sedation, coma, and death.
Intervention: | Reserve concomitant prescribing of these drugs for use in patients for whom alternative treatment options are inadequate. Limit dosages and durations to the minimum required. Follow patients closely for signs of respiratory depression and sedation [see Warnings and Precautions (5.4)].
Examples: | Benzodiazepines and other sedatives/hypnotics, anxiolytics, tranquilizers, muscle relaxants, general anesthetics, antipsychotics, other opioids, alcohol.

7.3 Serotonergic Drugs

The concomitant use of opioids with other drugs that affect the serotonergic neurotransmitter system, such as selective serotonin reuptake inhibitors (SSRIs), serotonin and norepinephrine reuptake inhibitors (SNRIs), tricyclic antidepressants (TCAs), triptans, 5-HT3 receptor antagonists, drugs that effect the serotonin neurotransmitter system (e.g., mirtazapine, trazodone, tramadol), and monoamine oxidase (MAO) inhibitors (those intended to treat psychiatric disorders and also others, such as linezolid and intravenous methylene blue), has resulted in serotonin syndrome.

If concomitant use is warranted, carefully observe the patient, particularly during treatment initiation and dose adjustment. Discontinue oxymorphone hydrochloride extended-release tablets if serotonin syndrome is suspected.

7.4 Interactions with Mixed Agonist/Antagonist and Partial Agonist Opioid Analgesics

Mixed agonist/antagonist analgesics (i.e., pentazocine, nalbuphine, and butorphanol), and partial agonists (buprenorphine) may reduce the analgesic effect of oxymorphone hydrochloride extended-release tablets or precipitate withdrawal symptoms. Avoid the use of mixed agonist/antagonist and partial agonist analgesics in patients receiving oxymorphone hydrochloride extended-release tablets.

7.5 Muscle Relaxants

Oxymorphone may enhance the neuromuscular blocking action of skeletal muscle relaxants and produce an increased degree of respiratory depression. Monitor patients receiving muscle relaxants and oxymorphone hydrochloride extended-release tablets for signs of respiratory depression that may be greater than otherwise expected.

7.6 Cimetidine

Cimetidine can potentiate opioid-induced respiratory depression. Monitor patients for respiratory depression when oxymorphone hydrochloride extended-release tablets and cimetidine are used concurrently.

7.7 Anticholinergics

Anticholinergics or other medications with anticholinergic activity when used concurrently with opioid analgesics may result in increased risk of urinary retention and/or severe constipation, which may lead to paralytic ileus. Monitor patients for signs of respiratory and central nervous system depression when oxymorphone hydrochloride extended-release tablets are used concurrently with anticholinergic drugs.

8 USE IN SPECIFIC POPULATIONS

8.1 Pregnancy

Clinical Considerations

Fetal/neonatal adverse reactions

Prolonged use of opioid analgesics during pregnancy for medical or nonmedical purposes can result in physical dependence in the neonate and neonatal opioid withdrawal syndrome shortly after birth. Observe newborns for symptoms of neonatal opioid withdrawal syndrome, such as poor feeding, diarrhea, irritability, tremor, rigidity, and seizures, and manage accordingly [see Warnings and Precautions (5.3)].

Teratogenic Effects - Pregnancy Category C

There are no adequate and well-controlled studies in pregnant women. Oxymorphone hydrochloride extended-release tablets should be used during pregnancy only if the potential benefit justifies the potential risk to the fetus.

Oxymorphone hydrochloride administration did not cause malformations at any doses evaluated during developmental toxicity studies in rats (≤ 25 mg/kg/day) or rabbits (≤ 50 mg/kg/day). These doses are ~3-fold and ~12-fold the human dose of 40 mg every 12 hours, based on body surface area. There were no developmental effects in rats treated with 5 mg/kg/day or rabbits treated with 25 mg/kg/day. Fetal weights were reduced in rats and rabbits given doses of ≥ 10 mg/kg/day and 50 mg/kg/day, respectively. These doses are ~1.2-fold and ~12-fold the human dose of 40 mg every 12 hours based on body surface area, respectively. There were no effects of oxymorphone hydrochloride on intrauterine survival in rats at doses ≤ 25 mg/kg/day, or rabbits at ≤ 50 mg/kg/day in these studies (see Non-teratogenic Effects, below). In a study that was conducted prior to the establishment of Good Laboratory Practices (GLP) and not according to current recommended methodology, a single subcutaneous injection of oxymorphone hydrochloride on gestation day 8 was reported to produce malformations in offspring of hamsters that received 15.5-fold the human dose of 40 mg every 12 hours based on body surface area. This dose also produced 20% maternal lethality.

Non-teratogenic Effects

Oxymorphone hydrochloride administration to female rats during gestation in a pre- and postnatal developmental toxicity study reduced mean litter size (18%) at a dose of 25 mg/kg/day, attributed to an increased incidence of stillborn pups. An increase in neonatal death occurred at ≥ 5 mg/kg/day. Post-natal survival of the pups was reduced throughout weaning following treatment of the dams with 25 mg/kg/day. Low pup birth weight and decreased postnatal weight gain occurred in pups born to oxymorphone-treated pregnant rats given a dose of 25 mg/kg/day.

This dose is ~3-fold higher than the human dose of 40 mg every 12 hours on a body surface area basis.

8.2 Labor and Delivery

Opioids cross the placenta and may produce respiratory depression in neonates. Oxymorphone hydrochloride extended-release tablets are not for use in women during and immediately prior to labor, when shorter acting analgesics or other analgesic techniques are more appropriate. Opioid analgesics can prolong labor through actions that temporarily reduce the strength, duration, and frequency of uterine contractions. However this effect is not consistent and may be offset by an increased rate of cervical dilatation, which tends to shorten labor.

8.3 Nursing Mothers

It is not known whether oxymorphone is excreted in human milk. Because many drugs, including some opioids, are excreted in human milk, caution should be exercised when oxymorphone hydrochloride extended-release tablets are administered to a nursing woman. Monitor infants who may be exposed to oxymorphone hydrochloride extended-release tablets through breast milk for excess sedation and respiratory depression. Withdrawal symptoms can occur in breast-fed infants when maternal administration of an opioid analgesic is stopped, or when breast-feeding is stopped.

8.4 Pediatric Use

The safety and effectiveness of oxymorphone hydrochloride extended-release tablets in patients below the age of 18 years have not been established.

8.5 Geriatric Use

Of the total number of subjects in clinical studies of oxymorphone hydrochloride extended-release tablets, 27% were 65 and over, while 9% were 75 and over. No overall differences in effectiveness were observed between these subjects and younger subjects. There were several adverse events that were more frequently observed in subjects 65 and over compared to younger subjects. These adverse events included dizziness, somnolence, confusion, and nausea. On average, age greater than 65 years was associated with a 1.4-fold increase in oxymorphone AUC and a 1.5-fold increase in Cmax. Initiate dosing with oxymorphone hydrochloride extended-release tablets in patients 65 years of age and over using the 5 mg dose and monitor closely for signs of respiratory and central nervous system depression when initiating and titrating oxymorphone hydrochloride extended-release tablets. For patients on prior opioid therapy, start at 50% of the starting dose for a younger patient on prior opioids and titrate slowly.

8.6 Hepatic Impairment

Patients with mild hepatic impairment have an increase in oxymorphone bioavailability of 1.6-fold. In opioid-naïve patients with mild hepatic impairment, initiate oxymorphone hydrochloride extended-release tablets using the 5 mg dose and monitor closely for respiratory and central nervous system depression. Oxymorphone hydrochloride extended-release tablets are contraindicated for patients with moderate and severe hepatic impairment [see Contraindications (4), Warnings and Precautions (5.9), and Dosage and Administration (2.5)]. For patients on prior opioid therapy, start at the 50% of the dose for that a patient with normal hepatic function on prior opioids and titrate slowly.

8.7 Renal Impairment

Patients with moderate to severe renal impairment were shown to have an increase in oxymorphone bioavailability ranging from 57 to 65% [see Clinical Pharmacology (12.3)]. Start opioid-naïve patients with the 5 mg dose of oxymorphone hydrochloride extended-release tablets and titrate slowly while closely monitoring for respiratory and central nervous system depression [see Dosage and Administration (2.6)]. For patients on prior opioid therapy, start at 50% of the dose for a patient with normal renal function on prior opioids and titrate slowly.

8.8 Infertility

Chronic use of opioids may cause reduced fertility in females and males of reproductive potential. It is not known whether these effects on fertility are reversible [see Adverse Reactions (6.2)].

9 DRUG ABUSE AND DEPENDENCE

9.1 Controlled Substance

Oxymorphone hydrochloride extended-release tablets contain oxymorphone, a Schedule II controlled substance with an abuse liability similar to other opioids including fentanyl, hydromorphone, methadone, morphine, oxycodone and tapentadol. Oxymorphone hydrochloride extended-release tablets can be abused and is subject to criminal diversion [see Warnings and Precautions (5.1)].

The high drug content in extended release formulations adds to the risk of adverse outcomes from abuse and misuse.

9.2 Abuse

All patients treated with opioids require careful monitoring for signs of abuse and addiction, since use of opioid analgesic products carries the risk of addiction even under appropriate medical use.

Drug abuse is the intentional non-therapeutic use of an over-the-counter or prescription drug, even once, for its rewarding psychological or physiological effects. Drug abuse includes, but is not limited to the following examples: the use of a prescription or over-the counter drug to get "high", or the use of steroids for performance enhancement and muscle build up.

Drug addiction is a cluster of behavioral, cognitive, and physiological phenomena that develop after repeated substance use and include: a strong desire to take the drug, difficulties in controlling its use, persisting in its use despite harmful consequences, a higher priority given to drug use than to other activities and obligations, increased tolerance , and sometimes a physical withdrawal.

"Drug seeking" behavior is very common to addicts and drug abusers. Drug-seeking tactics include emergency calls or visits near the end of office hours, refusal to undergo appropriate examination, testing or referral, repeated claims of loss of prescriptions, tampering with prescriptions and reluctance to provide prior medical records or contact information for other treating physician(s). “Doctor shopping” (visiting multiple prescribers) to obtain additional prescriptions is common among drug abusers and people suffering from untreated addiction. Preoccupation with achieving adequate pain relief can be appropriate behavior in a patient with poor pain control.

Abuse and addiction are separate and distinct from physical dependence and tolerance. Physicians should be aware that addiction may not be accompanied by concurrent tolerance and symptoms of physical dependence in all addicts. In addition, abuse of opioids can occur in the absence of true addiction.

Oxymorphone hydrochloride extended-release tablets, like other opioids, can be diverted for non-medical use into illicit channels of distribution. Careful record-keeping of prescribing information, including quantity, frequency, and renewal requests as required by state law, is strongly advised.

Proper assessment of the patient, proper prescribing practices, periodic re-evaluation of therapy, and proper dispensing and storage are appropriate measures that help to reduce abuse of opioid drugs.

Risks Specific to Abuse of Oxymorphone Hydrochloride Extended-Release Tablets

Oxymorphone hydrochloride extended-release tablets are for oral use only. Abuse of oxymorphone hydrochloride extended-release tablets poses a risk of overdose and death. This risk is increased with concurrent abuse of oxymorphone hydrochloride extended-release tablets with alcohol and other substances. Taking cut, broken, chewed, crushed, or dissolved oxymorphone hydrochloride extended-release tablets enhances drug release and increases the risk of over dose and death.

Parenteral drug abuse is commonly associated with transmission of infectious diseases such as hepatitis and HIV.

9.3 Dependence

Both tolerance and physical dependence can develop during chronic opioid therapy. Tolerance is the need for increasing doses of opioids to maintain a defined effect such as analgesia (in the absence of disease progression or other external factors). Tolerance may occur to both the desired and undesired effects of drugs, and may develop at different rates for different effects.

Physical dependence results in withdrawal symptoms after abrupt discontinuation or a significant dose reduction of a drug. Withdrawal also may be precipitated through the administration of drugs with opioid antagonist activity, e.g., naloxone, nalmefene, mixed agonist/antagonist analgesics (pentazocine, butorphanol, nalbuphine), or partial agonists (buprenorphine). Physical dependence may not occur to a clinically significant degree until after several days to weeks of continued opioid usage.

Oxymorphone hydrochloride extended-release tablets should not be abruptly discontinued [see Dosage and Administration (2.3)]. If oxymorphone hydrochloride extended-release tablets are abruptly discontinued in a physically-dependent patient, an abstinence syndrome may occur. Some or all of the following can characterize this syndrome: restlessness, lacrimation, rhinorrhea, yawning, perspiration, chills, myalgia, and mydriasis. Other signs and symptoms also may develop, including: irritability, anxiety, backache, joint pain, weakness, abdominal cramps, insomnia, nausea, anorexia, vomiting, diarrhea, or increased blood pressure, respiratory rate, or heart rate.

Infants born to mothers physically dependent on opioids will also be physically dependent and may exhibit respiratory difficulties and withdrawal symptoms [see Use in Specific Populations (8.2)].

10 OVERDOSAGE

Clinical Presentation

Acute overdosage with oxymorphone is manifested by respiratory depression, somnolence progressing to stupor or coma, skeletal muscle flaccidity, cold and clammy skin, constricted pupils, and, sometimes, pulmonary edema, bradycardia, hypotension, and death. Marked mydriasis rather than miosis may be seen due to severe hypoxia in overdose situations.

Treatment of Overdose

In case of overdose, priorities are the re-establishment of a patent and protected airway and institution of assisted or controlled ventilation if needed. Employ other supportive measures (including oxygen, vasopressors) in the management of circulatory shock and pulmonary edema as indicated. Cardiac arrest or arrhythmias will require advanced life support techniques.

The opioid antagonists, naloxone or nalmefene, are specific antidotes to respiratory depression resulting from opioid overdose. Opioid antagonists should not be administered in the absence of clinically significant respiratory or circulatory depression secondary to oxymorphone overdose. Such agents should be administered cautiously to patients who are known, or suspected to be, physically dependent on oxymorphone hydrochloride extended-release tablets. In such cases, an abrupt or complete reversal of opioid effects may precipitate an acute withdrawal syndrome.

Because the duration of reversal would be expected to be less than the duration of action of oxymorphone in oxymorphone hydrochloride extended-release tablets, carefully monitor the patient until spontaneous respiration is reliably re-established. Oxymorphone hydrochloride extended-release tablets will continue to release oxymorphone adding to the oxymorphone load for up to 24 hours after administration, necessitating prolonged monitoring. If the response to opioid antagonists is suboptimal or not sustained, additional antagonist should be given as directed in the product’s prescribing information.

In an individual physically dependent on opioids, administration of an opioid receptor antagonist may precipitate an acute withdrawal. The severity of the withdrawal produced will depend on the degree of physical dependence and the dose of the antagonist administered. If a decision is made to treat serious respiratory depression in the physically dependent patient, administration of the antagonist should be begun with care and by titration with smaller than usual doses of the antagonist.

11 DESCRIPTION

Oxymorphone hydrochloride extended-release tablets are for oral use and contain oxymorphone, a semi-synthetic opioid analgesic. Oxymorphone hydrochloride extended-release tablets are supplied in 5 mg, 7.5 mg, 10 mg, 15 mg, 20 mg, 30 mg, and 40 mg tablet strengths for oral administration. The tablet strength describes the amount of oxymorphone hydrochloride, USP per tablet.

The tablets contain the following inactive ingredients: hydrophobic colloidal silica, hypromellose, polyethylene glycol, polyvinyl alcohol, silicified microcrystalline cellulose, sodium stearyl fumarate, talc, and titanium dioxide.

In addition, the 5 mg and 30 mg tablets contain FD&C red No. 40. The 7.5 mg tablets contain ferric oxide black, and ferric oxide yellow. The 10 mg tablets contain ferric oxide yellow and FD&C yellow No. 6. The 20 mg tablets contain D&C yellow No. 10, FD&C blue No. 1, and FD&C yellow No. 6. The 30 mg tablets contain FD&C blue No. 1 and FD&C yellow No. 6. The 40 mg tablets contain D&C yellow No. 10 and FD&C yellow No. 6.

The chemical name of oxymorphone hydrochloride is 4, 5α -epoxy-3, 14-dihydroxy-17-methylmorphinan-6-one hydrochloride, a white to off-white powder, which is sparingly soluble in alcohol, but freely soluble in water. The molecular weight of oxymorphone hydrochloride is 337.80. The molecular formula of oxymorphone hydrochloride is C17H19NO4.HCl. The pKa1 and pKa2 of oxymorphone at 37° C are 8.17 and 9.54, respectively. The octanol/aqueous partition coefficient at 37° C and pH 7.4 is 0.98.

The structural formula for oxymorphone hydrochloride is as follows:

12 CLINICAL PHARMACOLOGY

12.1 Mechanism of Action

Oxymorphone, an opioid agonist, is relatively selective for the mu receptor, although it can interact with other opioid receptors at higher doses.

The precise mechanism of analgesia, the principal therapeutic action of oxymorphone, is unknown. Specific central nervous system (CNS) opiate receptors and endogenous compounds with morphine-like activity have been identified throughout the brain and spinal cord and are likely to play a role in the expression and perception of analgesic effects. In addition, opioid receptors have also been identified within the peripheral nervous system (PNS). The role that these receptors play in these drugs’ analgesic effects is unknown.

12.2 Pharmacodynamics

Concentration-Efficacy Relationships

The minimum effective plasma concentration of oxymorphone for analgesia varies widely among patients, especially among patients who have been previously treated with agonist opioids. As a result, individually titrate patients to achieve a balance between therapeutic and adverse effects. The minimum effective analgesic concentration of oxymorphone for any individual patient may increase over time due to an increase in pain, progression of disease, development of a new pain syndrome and/or potential development of analgesic tolerance.

Concentration-Adverse Experience Relationships

There is a general relationship between increasing opioid plasma concentration and increasing frequency of adverse experiences such as nausea, vomiting, CNS effects, and respiratory depression.

CNS Depressant/Alcohol Interaction

Additive pharmacodynamic effects may be expected when oxymorphone hydrochloride extended-release tablets are used in conjunction with alcohol, other opioids, or illicit drugs that cause central nervous system depression.

Effects on the Central Nervous System (CNS)

The principal therapeutic action of oxymorphone is analgesia. Oxymorphone causes respiratory depression, in part by a direct effect on the brainstem respiratory centers. The respiratory depression involves a reduction in the responsiveness of the brain stem respiratory centers to both increases in carbon dioxide tension and electrical stimulation. Oxymorphone depresses the cough reflex by direct effect on the cough center in the medulla.

Oxymorphone causes miosis, even in total darkness. Pinpoint pupils are a sign of opioid overdose but are not pathognomonic (e.g., pontine lesions of hemorrhagic or ischemic origin may produce similar findings). Marked mydriasis rather than miosis may be seen with hypoxia in overdose situations [see Overdosage (10)]. Other therapeutic effects of oxymorphone include anxiolysis, euphoria, and feeling of relaxation, drowsiness and changes in mood.

Effects on the Gastrointestinal Tract and on Other Smooth Muscle

Gastric, biliary and pancreatic secretions are decreased by oxymorphone. Oxymorphone causes a reduction in motility and is associated with an increase in tone in the antrum of the stomach and duodenum. Digestion of food in the small intestine is delayed and propulsive contractions are decreased. Propulsive peristaltic waves in the colon are decreased, while tone is increased to the point of spasm. The end result is constipation. Oxymorphone can cause a marked increase in biliary tract pressure as a result of spasm of the sphincter of Oddi, and transient elevations in serum amylase. Oxymorphone may also cause spasm of the sphincter of the urinary bladder.

Effects on the Cardiovascular System

Oxymorphone produces peripheral vasodilation which may result in orthostatic hypotension. Release of histamine can occur and may contribute to opioid-induced hypotension. Manifestations of histamine release may include orthostatic hypotension, pruritus, flushing, red eyes, and sweating.

Effects on the Endocrine System

Opioid agonists have been shown to have a variety of effects on the secretion of hormones. Opioids inhibit the secretion of ACTH, cortisol, and luteinizing hormone (LH) in humans. They also stimulate prolactin, growth hormone (GH) secretion, and pancreatic secretion of insulin and glucagon.

Effects on the Immune System

Opioids have been shown to have a variety of effects on components of the immune system in in vitro and animal models. The clinical significance of these findings is unknown.

12.3 Pharmacokinetics

Absorption

The absolute oral bioavailability of oxymorphone is approximately 10%.

Steady-state levels are achieved after three days of multiple dose administration. Under both single-dose and steady-state conditions, dose proportionality has been established for the 5 mg, 10 mg, 20 mg, and 40 mg doses of oxymorphone hydrochloride extended-release tablets, for both peak plasma levels (Cmax) and extent of absorption (AUC) (see Table 4).

Table 4: Mean (± SD) Oxymorphone Hydrochloride Extended-Release Tablets Pharmacokinetic Parameters
Regimen | Dosage | Cmax (ng/mL) | AUC (ng•hr/mL) | T1/2 (hr)
Single Dose | 5 mg | 0.27 ± 0.13 | 4.54 ± 2.04 | 11.30 ± 10.81
Single Dose | 10 mg | 0.65 ± 0.29 | 8.94 ± 4.16 | 9.83 ± 5.68
Single Dose | 20 mg | 1.21 ± 0.77 | 17.81 ± 7.22 | 9.89 ± 3.21
Single Dose | 40 mg | 2.59 ± 1.65 | 37.90 ± 16.20 | 9.35 ± 2.94
Multiple Dosea | 5 mg | 0.70 ± 0.55 | 5.60 ± 3.87 | NA
Multiple Dosea | 10 mg | 1.24 ± 0.56 | 9.77 ± 3.52 | NA
Multiple Dosea | 20 mg | 2.54 ± 1.35 | 19.28 ± 8.32 | NA
Multiple Dosea | 40 mg | 4.47 ± 1.91 | 36.98 ± 13.53 | NA
NA = not applicable a Results after 5 days of q12h dosing.

Food Effect

Two studies examined the effect of food on the bioavailability of single doses of 20 and 40 mg of oxymorphone hydrochloride extended-release tablets in healthy volunteers. In both studies, after the administration of oxymorphone hydrochloride extended-release tablets, the Cmax was increased by approximately 50% in fed subjects compared to fasted subjects. A similar increase in Cmax was also observed with oxymorphone solution.

The AUC was unchanged in one study and increased by approximately 18% in the other study in fed subjects following the administration of oxymorphone hydrochloride extended-release tablets. Examination of the AUC suggests that most of the difference between fed and fasting conditions occurs in the first four hours after dose administration. After oral dosing with a single dose of 40 mg, a peak oxymorphone plasma level of 2.8 ng/mL is achieved at 1 hour in fasted subjects and a peak of 4.25 ng/mL is achieved at 2 hours in fed subjects and that beyond the 12 hour time point, there is very little difference in the curves. As a result, oxymorphone hydrochloride extended-release tablets should be dosed at least one hour prior to or two hours after eating [see Dosage and Administration (2.1, 2.2)].

Distribution

Formal studies on the distribution of oxymorphone in various tissues have not been conducted. Oxymorphone is not extensively bound to human plasma proteins; binding is in the range of 10% to 12%.

Metabolism

Oxymorphone is highly metabolized, principally in the liver, and undergoes reduction or conjugation with glucuronic acid to form both active and inactive metabolites. The two major metabolites of oxymorphone are oxymorphone-3-glucuronide and 6-OH-oxymorphone. The mean plasma AUC for oxymorphone-3-glucuronide is approximately 90-fold higher than the parent compound. The pharmacologic activity of the glucuronide metabolite has not been evaluated. 6-OH-oxymorphone has been shown in animal studies to have analgesic bioactivity. The mean plasma 6-OH-oxymorphone AUC is approximately 70% of the oxymorphone AUC following single oral doses, but is essentially equivalent to the parent compound at steady-state.

Excretion

Because oxymorphone is extensively metabolized, < 1% of the administered dose is excreted unchanged in the urine. On average, 33% to 38% of the administered dose is excreted in the urine as oxymorphone-3-glucuronide and less than 1% excreted as 6-OH-oxymorphone in subjects with normal hepatic and renal function. In animals given radiolabeled oxymorphone, approximately 90% of the administered radioactivity was recovered within 5 days of dosing. The majority of oxymorphone-derived radioactivity was found in the urine and feces.

Specific Populations

Geriatric Patients

The steady-state plasma concentrations of oxymorphone, 6-OH-oxymorphone, and oxymorphone-3-glucuronide are approximately 40% higher in elderly subjects (≥ 65 years of age) than in young subjects (18 to 40 years of age). On average, age greater than 65 years was associated with a 1.4-fold increase in oxymorphone AUC and a 1.5-fold increase in Cmax. This observation does not appear related to a difference in body weight, metabolism, or excretion of oxymorphone [see Use in Specific Populations (8.5)].

Gender

The effect of gender was evaluated following single- and multiple-doses of oxymorphone hydrochloride extended-release tablets in male and female adult volunteers. There was a consistent tendency for female subjects to have slightly higher AUCss and Cmax values than male subjects; however, gender differences were not observed when AUCss and Cmax were adjusted by body weight.

Hepatic Impairment

The bioavailability of orally administered oxymorphone is markedly increased in patients with moderate to severe liver disease. The disposition of oxymorphone was compared in six patients with mild, five patients with moderate, and one patient with severe hepatic impairment and 12 subjects with normal hepatic function. The bioavailability of oxymorphone was increased by 1.6-fold in patients with mild hepatic impairment and by 3.7-fold in patients with moderate hepatic impairment. In one patient with severe hepatic impairment, the bioavailability was increased by 12.2-fold. The half-life of oxymorphone was not significantly affected by hepatic impairment.

Renal Impairment

Data from a pharmacokinetic study involving 24 patients with renal dysfunction show an increase of 26%, 57%, and 65% in oxymorphone bioavailability in mild (creatinine clearance 51 to 80 mL/min; n = 8), moderate (creatinine clearance 30 to 50 mL/min; n = 8), and severe (creatinine clearance < 30 mL/min; n = 8) patients, respectively, compared to healthy controls.

Drug Interaction/Alcohol Interaction

An in vivo study of the effect of alcohol (40%, 20%, 4% and 0%) on the bioavailability of a single dose of 40 mg of oxymorphone hydrochloride extended-release tablets in healthy, fasted volunteers demonstrated a highly variable effect on Cmax with concomitant administration of alcohol and oxymorphone hydrochloride extended-release tablets. The change in Cmax ranged from a decrease of 50% to an increase of 270% across all conditions studied. Following administration of 240 mL of 40% ethanol, the Cmax increased on average by 70% and up to 270% in individual subjects. Following the concomitant administration of 240 mL of 20% ethanol, the Cmax increased on average by 31% and up to 260% in individual subjects. Following the concomitant administration of 240 mL of 4% ethanol, the Cmax increased 7% on average and by as much as 110% for individual subjects. After oral dosing with a single dose of 40 mg in fasted subjects, the mean peak oxymorphone plasma level is 2.4 ng/mL and the median Tmax is 2 hours. Following co-administration of oxymorphone hydrochloride extended-release tablets and alcohol (240 mL of 40% ethanol) in fasted subjects, the mean peak oxymorphone level is 3.9 ng/mL and the median Tmax is 1.5 hours (range 0.75 to 6 hours). The oxymorphone mean AUC was 13% higher after co-administration of 240 mL of 40% alcohol. The AUC was essentially unaffected in subjects following the co-administration of oxymorphone hydrochloride extended-release tablets and ethanol (240 mL of 20% or 4% ethanol).

In vitro studies have demonstrated that oxymorphone hydrochloride extended-release tablets do not release oxymorphone more rapidly in 500 mL of 0.1N HCl solutions containing ethanol (4%, 20%, and 40%),

Instruct patients to avoid use of alcohol when taking oxymorphone hydrochloride extended-release tablets.

In vitro studies revealed little to no biotransformation of oxymorphone to 6-OH-oxymorphone by any of the major cytochrome P450 (CYP P450) isoforms at therapeutically relevant oxymorphone plasma concentrations.

No inhibition of any of the major CYP P450 isoforms was observed when oxymorphone was incubated with human liver microsomes at concentrations of ≤ 15.1 mcg/mL. An inhibition of CYP3A4 activity occurred at oxymorphone concentrations ≥ 45.3 mcg/mL. Therefore, it is not expected that oxymorphone, or its metabolites will act as inhibitors of any of the major CYP P450 enzymes in vivo.

Increases in the activity of the CYP 2C9 and CYP 3A4 isoforms occurred when oxymorphone was incubated with human hepatocytes. However, clinical drug interaction studies with oxymorphone hydrochloride extended-release tablets showed no induction of CYP450 3A4 or 2C9 enzyme activity, indicating that no dose adjustment for CYP 3A4- or 2C9-mediated drug-drug interactions is required.

13 NONCLINICAL TOXICOLOGY

13.1 Carcinogenesis, Mutagenesis, Impairment of Fertility

Carcinogenesis

Long-term studies have been completed to evaluate the carcinogenic potential of oxymorphone in both Sprague-Dawley rats and CD-1 mice. Oxymorphone HCl was administered to Sprague-Dawley rats (2.5, 5, and 10 mg/kg/day in males and 5, 10, and 25 mg/kg/day in females) for 2 years by oral gavage. The systemic drug exposure (AUC ng•h/mL) at the 10 mg/kg/day in male rats was 0.34-fold and at the 25 mg/kg/day dose in female rats was 1.5-fold the human exposure at a dose of 260 mg/day. No evidence of carcinogenic potential was observed in rats. Oxymorphone was administered to CD-1 mice (10, 25, 75 and 150 mg/kg/day) for 2 years by oral gavage. The systemic drug exposure (AUC ng•h/mL) at the 150 mg/kg/day dose in mice was 14.5-fold (in males) and 17.3-fold (in females) times the human exposure at a dose of 260 mg/day. No evidence of carcinogenic potential was observed in mice.

Mutagenesis

Oxymorphone hydrochloride was not mutagenic when tested in the in vitro bacterial reverse mutation assay (Ames test) at concentrations of ≤ 5270 mcg/plate, or in an in vitro mammalian cell chromosome aberration assay performed with human peripheral blood lymphocytes at concentrations ≤ 5000 mcg/mL with or without metabolic activation. Oxymorphone hydrochloride tested positive in both the rat and mouse in vivo micronucleus assays. An increase in micronucleated polychromatic erythrocytes occurred in mice given doses ≥ 250 mg/kg and in rats given doses of 20 and 40 mg/kg. A subsequent study demonstrated that oxymorphone hydrochloride was not aneugenic in mice following administration of up to 500 mg/kg. Additional studies indicate that the increased incidence of micronucleated polychromatic erythrocytes in rats may be secondary to increased body temperature following oxymorphone administration. Doses associated with increased micronucleated polychromatic erythrocytes also produce a marked, rapid increase in body temperature. Pretreatment of animals with sodium salicylate minimized the increase in body temperature and prevented the increase in micronucleated polychromatic erythrocytes after administration of 40 mg/kg oxymorphone.

Impairment of Fertility

Oxymorphone hydrochloride did not affect reproductive function or sperm parameters in male rats at any dose tested (≤ 50 mg/kg/day). The highest dose tested is ~6-fold the human dose of 40 mg every 12 hours, based on body surface area. In female rats, an increase in the length of the estrus cycle and decrease in the mean number of viable embryos, implantation sites and corpora lutea were observed at doses of oxymorphone ≥ 10 mg/kg/day. The dose of oxymorphone associated with reproductive findings in female rats is 1.2-fold the human dose of 40 mg every 12 hours based on a body surface area. The dose of oxymorphone that produced no adverse effects on reproductive findings in female rats is 0.6-fold the human dose of 40 mg every 12 hours on a body surface area basis.

14 CLINICAL STUDIES

The efficacy and safety of oxymorphone hydrochloride extended-release tablets have been evaluated in double-blind, controlled clinical trials in opioid-naïve and opioid-experienced patients with moderate to severe pain including low back pain.

12-Week Study in Opioid-Naïve Patients with Low Back Pain

Patients with chronic low back pain who were suboptimally responsive to their non-opioid therapy entered a 4-week, open-label dose titration phase. Patients initiated therapy with two days of treatment with oxymorphone hydrochloride extended-release tablets 5 mg, every 12 hours. Thereafter, patients were titrated to a stabilized dose, at increments of 5 to 10 mg every 12 hours every 3 to 7 days. Of the patients who were able to stabilize within the Open-Label Titration Period, the mean ± SD VAS score at Screening was 69.4 ± 11.8 mm and at Baseline (beginning of Double-Blind Period) were 18.5 ± 11.2 mm and 19.3 ± 11.3 mm for the oxymorphone ER and placebo groups, respectively. Sixty three percent of the patients enrolled were able to titrate to a tolerable dose and were randomized into a 12-week double-blind treatment phase with placebo or their stabilized dose of oxymorphone hydrochloride extended-release tablets. The mean ± SD stabilized doses were 39.2 ± 26.4 mg and 40.9 ± 25.3 mg for the oxymorphone hydrochloride extended-release tablets and placebo groups, respectively; total daily doses ranged from 10 to 140 mg. During the first 4 days of double-blind treatment patients were allowed an unlimited number of oxymorphone hydrochloride tablets, an immediate-release (IR) formulation of oxymorphone, 5 mg tablets, every 4 to 6 hours as supplemental analgesia; thereafter the number of oxymorphone hydrochloride tablets was limited to two tablets per day. This served as a tapering method to minimize opioid withdrawal symptoms in placebo patients. Sixty-eight percent of patients treated with oxymorphone hydrochloride extended-release tablets completed the 12-week treatment compared to 47% of patients treated with placebo. Oxymorphone hydrochloride extended-release tablets provided superior analgesia compared to placebo. The analgesic effect of oxymorphone hydrochloride extended-release tablets was maintained throughout the double-blind treatment period in 89% of patients who completed the study. These patients reported a decrease, no change, or a ≤ 10 mm increase in VAS score from Day 7 until the end of the study.

The proportion of patients with various degrees of improvement from screening to study endpoint is shown in Figure 1. The figure is cumulative, so that patients whose change from baseline is, for example, 30%, are also included at every level of improvement below 30%. Patients who did not complete the study were assigned 0% improvement.

Figure 1: Percent Reduction in Average Pain Intensity from Screening to Final Visit

12-Week Study in Opioid-Experienced Patients with Low Back Pain

Patients on chronic opioid therapy entered a 4-week, open-label titration phase with oxymorphone hydrochloride extended-release tablets dosed every 12 hours at an approximated equianalgesic dose of their pre-study opioid medication. Of the patients who were able to stabilize within the Open-Label Titration Period, the mean ± SD VAS score at Screening was 69.5 ± 17 mm and at Baseline (beginning of Double-Blind Period) were 23.9 ± 12.1 mm and 22.2 ± 10.8 mm for the oxymorphone ER and placebo groups, respectively. Stabilized patients entered a 12-week double-blind treatment phase with placebo or their stabilized dose of oxymorphone hydrochloride extended-release tablets. The mean ± SD stabilized doses were 80.9 ± 59.3 mg and 93.3 ± 61.3 mg for the oxymorphone hydrochloride extended-release tablets and placebo groups, respectively; total daily doses ranged from 20 to 260 mg. During the first 4 days of double-blind treatment, patients were allowed an unlimited number of oxymorphone hydrochloride 5 mg tablets, every 4 to 6 hours as supplemental analgesia; thereafter the number of oxymorphone hydrochloride tablets was limited to two tablets per day. This served as a tapering method to minimize opioid withdrawal symptoms in placebo patients. Fifty seven percent of patients were titrated to a stabilized dose within approximately 4 weeks of oxymorphone hydrochloride extended-release tablets dose titration. Seventy percent of patients treated with oxymorphone hydrochloride extended-release tablets and 26% of patients treated with placebo completed the 12-week treatment. Oxymorphone hydrochloride extended-release tablets provided superior analgesia compared to placebo. The analgesic effect of oxymorphone hydrochloride extended-release tablets was maintained throughout the double-blind treatment period in 80 % of patients who completed the study. These patients reported a decrease, no change, or a ≤ 10 mm increase in VAS score from Day 7 until the end of the study.

The proportion of patients with various degrees of improvement from screening to study endpoint is shown in Figure 2. The figure is cumulative, so that patients whose change from baseline is, for example, 30%, are also included at every level of improvement below 30%. Patients who did not complete the study were assigned 0% improvement.

Figure 2: Percent Reduction in Average Pain Intensity from Screening to Final Visit

16 HOW SUPPLIED/STORAGE AND HANDLING

Oxymorphone hydrochloride extended-release tablets are supplied as follows:

5 mg

Pink to light pink, round, biconvex film-coated tablets, debossed with ‘RH 29’ on one side and plain on the other side.

NDC 63304-218-30 Bottles of 30 with child-resistant closure

NDC 63304-218-05 Bottles of 500

7.5 mg

Gray to light gray, round, biconvex film-coated tablets, debossed with ‘RI 36’ on one side and plain on the other side.

NDC 63304-219-30 Bottles of 30 with child-resistant closure

NDC 63304-219-05 Bottles of 500

10 mg

Orange to light orange, round, biconvex film-coated tablets, debossed with ‘RH 30’ on one side and plain on the other side.

NDC 63304-220-30 Bottles of 30 with child-resistant closure

NDC 63304-220-05 Bottles of 500

15 mg

White to off-white, round, biconvex film-coated tablets, debossed with ‘RI 37’ on one side and plain on the other side.

NDC 63304-221-30 Bottles of 30 with child-resistant closure

NDC 63304-221-05 Bottles of 500

20 mg

Green to light green, round, biconvex film-coated tablets, debossed with ‘RH 31’ on one side and plain on the other side.

NDC 63304-222-30 Bottles of 30 with child-resistant closure

NDC 63304-222-05 Bottles of 500

30 mg

Reddish brown, round, biconvex film-coated tablets, debossed with ‘RI 38’ on one side and plain on the other side.

NDC 63304-223-30 Bottles of 30 with child-resistant closure

NDC 63304-223-05 Bottles of 500

40 mg

Yellow to light yellow, round, biconvex film-coated tablets, debossed with ‘RH 32’ on one side and plain on the other side.

NDC 63304-224-30 Bottles of 30 with child-resistant closure

NDC 63304-224-05 Bottles of 500

Store at 20° - 25° C (68° - 77° F) [See USP Controlled Room Temperature].

Dispense in tight container as defined in the USP, with a child-resistant closure (as required).

17 PATIENT COUNSELING INFORMATION

Advise the patient to read the FDA-approved patient labeling (Medication Guide).

Addiction, Abuse, and Misuse

Inform patients that the use of oxymorphone hydrochloride extended-release tablets, even when taken as recommended, can result in addiction, abuse, and misuse, which can lead to overdose or death [see Warnings and Precautions (5.1)]. Instruct patients not to share oxymorphone hydrochloride extended-release tablets with others and to take steps to protect oxymorphone hydrochloride extended-release tablets from theft or misuse.

Life-threatening Respiratory Depression

Inform patients of the risk of life-threatening respiratory depression, including information that the risk is greatest when starting oxymorphone hydrochloride extended-release tablets or when the dose is increased, and that it can occur even at recommended doses [see Warnings and Precautions (5.2)]. Advise patients how to recognize respiratory depression and to seek medical attention if breathing difficulties develop.

Accidental Ingestion

Inform patients that accidental ingestion, especially in children, may result in respiratory depression or death [see Warnings and Precautions (5.2)]. Instruct patients to take steps to store oxymorphone hydrochloride extended-release tablets securely to dispose of unused oxymorphone hydrochloride extended-release tablets by flushing the tablets down the toilet.

Neonatal Opioid Withdrawal Syndrome

Inform female patients of reproductive potential that prolonged use of oxymorphone hydrochloride extended-release tablets during pregnancy can result in neonatal opioid withdrawal syndrome, which may be life-threatening if not recognized and treated [see Warnings and Precautions (5.3)].

Interactions with Benzodiazepines and Other CNS Depressants

Inform patients and caregivers that potentially fatal additive effects may occur if oxymorphone hydrochloride extended-release tablets are used with benzodiazepines or other CNS depressants, including alcohol, and not to use these concomitantly unless supervised by a health care provider [see Warnings and Precautions (5.4), Drug Interactions (7)].

Anaphylaxis. Angioedema, and Other Hypersensitivity Reactions

Inform patients that anaphylaxis and other hypersensitivity reactions have been reported with ingredients contained in oxymorphone hydrochloride extended-release tablets. Advise patients how to recognize such a reaction and when to seek medical attention [see Contraindications (4), Warnings and Precautions (5. 7), Adverse Reactions (6)].

Serotonin Syndrome

Inform patients that oxymorphone hydrochloride extended-release tablets could cause a rare but potentially life-threatening condition resulting from concomitant administration of serotonergic drugs. Warn patients of the symptoms of serotonin syndrome and to seek medical attention right away if symptoms develop. Instruct patients to inform their physicians if they are taking, or plan to take serotonergic medications [see Drug Interactions (7.3)].

Adrenal Insufficiency

Inform patients that oxymorphone hydrochloride extended-release tablets could cause adrenal insufficiency, a potentially life‑threatening condition. Adrenal insufficiency may present with non-specific symptoms and signs such as nausea, vomiting, anorexia, fatigue, weakness, dizziness, and low blood pressure. Advise patients to seek medical attention if they experience a constellation of these symptoms [see Warnings and Precautions (5.8)].

Important Administration Instructions

Instruct patients how to properly take oxymorphone hydrochloride extended-release tablets, including the following:

- Swallowing oxymorphone hydrochloride extended-release tablets whole
- Not crushing, chewing, or dissolving the tablets
- Using oxymorphone hydrochloride extended-release tablets exactly as prescribed to reduce the risk of life-threatening adverse reactions (e.g., respiratory depression)
- Not discontinuing oxymorphone hydrochloride extended-release tablets without first discussing the need for a tapering regimen with the prescriber

Hypotension

Inform patients that oxymorphone hydrochloride extended-release tablets may cause orthostatic hypotension and syncope. Instruct patients how to recognize symptoms of low blood pressure and how to reduce the risk of serious consequences should hypotension occur (e.g., sit or lie down, carefully rise from a sitting or lying position).

Driving or Operating Heavy Machinery

Inform patients that oxymorphone hydrochloride extended-release tablets may impair the ability to perform potentially hazardous activities such as driving a car or operating heavy machinery. Advise patients not to perform such tasks until they know how they will react to the medication.

Constipation

Advise patients of the potential for severe constipation, including management instructions and when to seek medical attention.

Pregnancy

Advise female patients that oxymorphone hydrochloride extended-release tablets can cause fetal harm and to inform the prescriber if they are pregnant or plan to become pregnant.

Disposal of Unused Oxymorphone Hydrochloride Extended-Release Tablets

Advise patients to flush the unused tablets down the toilet when oxymorphone hydrochloride extended-release tablets are no longer needed.

MEDICATION GUIDE

OXYMORPHONE HYDROCHLORIDE EXTENDED-RELEASE TABLETS, FOR ORAL USE, CII

Rx only

Oxymorphone hydrochloride extended-release tablets are:

- A strong prescription pain medicine that contains an opioid (narcotic) that is used to manage pain severe enough to require daily around-the-clock, long-term treatment with an opioid, when other pain treatments such as non-opioid pain medicines or immediate-release opioid medicines do not treat your pain well enough or you cannot tolerate them.
- A long-acting (extended-release) opioid pain medicine that can put you at risk for overdose and death. Even if you take your dose correctly as prescribed you are at risk for opioid addiction, abuse, and misuse that can lead to death.
- Not for use to treat pain that is not around-the-clock.

Important information about oxymorphone hydrochloride extended-release tablets:

- Get emergency help right away if you take too much oxymorphone hydrochloride extended-release tablets (overdose). When you first start taking oxymorphone hydrochloride extended-release tablets, when your dose is changed, or if you take too much (overdose), serious or life-threatening breathing problems that can lead to death may occur.
- Taking oxymorphone hydrochloride extended-release tablets with other opioid medicines, benzodiazepines, alcohol, or other central nervous system depressants (including street drugs) can cause severe drowsiness, decreased awareness, breathing problems, coma, and death.
- Never give anyone your oxymorphone hydrochloride extended-release tablets. They could die from taking it. Store oxymorphone hydrochloride extended-release tablets away from children and in a safe place to prevent stealing or abuse. Selling or giving away oxymorphone hydrochloride extended-release tablets is against the law.

Do not take oxymorphone hydrochloride extended-release tablets if you have:

- severe asthma, trouble breathing, or other lung problems.
- a bowel blockage or have narrowing of the stomach or intestines.

Before taking oxymorphone hydrochloride extended-release tablets, tell your healthcare provider if you have a history of:

- head injury, seizures

- liver, kidney, thyroid problems

- problems urinating

- pancreas or gallbladder problems

- abuse of street or prescription drugs, alcohol addiction, or mental health problems.

Tell your healthcare provider if you are:

- pregnant or planning to become pregnant. Prolonged use of oxymorphone hydrochloride extended-release tablets during pregnancy can cause withdrawal symptoms in your newborn baby that could be life-threatening if not recognized and treated.
- breastfeeding. Oxymorphone hydrochloride passes into breast milk and may harm your baby.
- taking prescription or over-the-counter medicines, vitamins, or herbal supplements. Taking oxymorphone hydrochloride extended-release tablets with certain other medicines can cause serious side effects.

When taking oxymorphone hydrochloride extended-release tablets:

- Do not change your dose. Take oxymorphone hydrochloride extended-release tablets exactly as prescribed by your healthcare provider.
- Take your prescribed dose every 12 hours at the same time every day on an empty stomach, at least 1 hour before or 2 hours after meals. Do not take more than your prescribed dose in 24 hours. If you miss a dose, take your next dose at your usual time.
- Swallow oxymorphone hydrochloride extended-release tablets whole. Do not cut, break, chew, crush, dissolve, snort, or inject oxymorphone hydrochloride extended-release tablets because this may cause you to overdose and die.
- Call your healthcare provider if the dose you are taking does not control your pain.
- Do not stop taking oxymorphone hydrochloride extended-release tablets without talking to your healthcare provider.
- After you stop taking oxymorphone hydrochloride extended-release tablets, flush any unused tablets down the toilet.

While taking oxymorphone hydrochloride extended-release tablets DO NOT:

- Drive or operate heavy machinery, until you know how oxymorphone hydrochloride extended-release tablets affect you. Oxymorphone hydrochloride extended-release tablets can make you sleepy, dizzy, or lightheaded.
- Drink alcohol or use prescription or over-the-counter medicines that contain alcohol. Using products containing alcohol during treatment with oxymorphone hydrochloride extended-release tablets may cause you to overdose and die.

The possible side effects of oxymorphone hydrochloride extended-release tablets:

- constipation, nausea, sleepiness, vomiting, tiredness, headache, dizziness, abdominal pain. Call your healthcare provider if you have any of these symptoms and they are severe.

Get emergency medical help if you have:

- trouble breathing, shortness of breath, fast heartbeat, chest pain, swelling of your face, tongue, throat, or hands, hives, itching, rash, extreme drowsiness, light-headedness when changing positions, feeling faint, agitation, high body temperature, trouble walking, stiff muscles, or mental changes such as confusion.

These are not all the possible side effects of oxymorphone hydrochloride extended-release tablets. Call your doctor for medical advice about side effects. You may report side effects to FDA at 1-800-FDA-1088. For more information go to dailymed.nlm.nih.gov

This Medication Guide has been approved by the U.S. Food and Drug Administration.

Manufactured for:

Ranbaxy Pharmaceuticals Inc.

Jacksonville, FL 32257 USA

www.ranbaxyusa.com or call 1-888-726-2299

September 2016 FDA-06

PACKAGE LABEL. PRINCIPAL DISPLAY PANEL

RANBAXY

NDC 63304-218-30

Twice-A-Day (every 12 hours)

OXYMORPHONE HCl EXTENDED-RELEASE TABLETS, CII

5 mg

DISPENSE ACCOMPANYING MEDICATION GUIDE TO EACH PATIENT

Rx only 30 Tablets

Package/Label Display Panel

RANBAXY

NDC 63304-219-30

Twice-A-Day (every 12 hours)

OXYMORPHONE HCl EXTENDED-RELEASE TABLETS, CII

7.5 mg

DISPENSE ACCOMPANYING MEDICATION GUIDE TO EACH PATIENT

Rx only 30 Tablets

Package/Label Display Panel

RANBAXY

NDC 63304-220-30

Twice-A-Day (every 12 hours)

OXYMORPHONE HCl EXTENDED-RELEASE TABLETS, CII

10 mg

DISPENSE ACCOMPANYING MEDICATION GUIDE TO EACH PATIENT

Rx only 30 Tablets

Package/Label Display Panel

RANBAXY

NDC 63304-221-30

Twice-A-Day (every 12 hours)

OXYMORPHONE HCl EXTENDED-RELEASE TABLETS, CII

15 mg

DISPENSE ACCOMPANYING MEDICATION GUIDE TO EACH PATIENT

Rx only 30 Tablets

Package/Label Display Panel

RANBAXY

NDC 63304-222-30

Twice-A-Day (every 12 hours)

OXYMORPHONE HCl EXTENDED-RELEASE TABLETS, CII

20 mg

DISPENSE ACCOMPANYING MEDICATION GUIDE TO EACH PATIENT

Rx only 30 Tablets

Package/Label Display Panel

RANBAXY

NDC 63304-223-30

Twice-A-Day (every 12 hours)

OXYMORPHONE HCl EXTENDED-RELEASE TABLETS, CII

30 mg

DISPENSE ACCOMPANYING MEDICATION GUIDE TO EACH PATIENT

Rx only 30 Tablets

Package/Label Display Panel

RANBAXY

NDC 63304-224-30

Twice-A-Day (every 12 hours)

OXYMORPHONE HCl EXTENDED-RELEASE TABLETS, CII

40 mg

DISPENSE ACCOMPANYING MEDICATION GUIDE TO EACH PATIENT

Rx only 30 Tablets